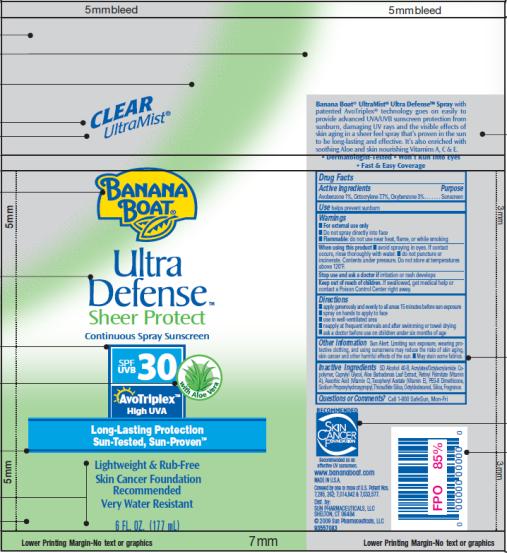 DRUG LABEL: Banana Boat Ultra Defense Sheer Protect SPF 30
NDC: 17630-2029 | Form: SPRAY
Manufacturer: Accra-Pac, Inc.
Category: otc | Type: HUMAN OTC DRUG LABEL
Date: 20100327

ACTIVE INGREDIENTS: AVOBENZONE 0.01 mL/1 mL; OCTOCRYLENE 0.077 mL/1 mL; OXYBENZONE 0.03 mL/1 mL
INACTIVE INGREDIENTS: CAPRYLYL GLYCOL; ALOE VERA LEAF; VITAMIN A PALMITATE; ASCORBIC ACID; .ALPHA.-TOCOPHEROL ACETATE, D-; OCTYLDODECANOL; SILICON DIOXIDE

Banana Boat Ultra Defense Sheer Protect SPF 30

Drug Facts

Active Ingredients

Avobenzone 0.01mL / 1mL

Octocrylene 0.077mL / 1mL

Oxybenzone 0.03mL / 1mL

Purpose

Sunscreen

Use

helps prevent sunburn

Warnings

- For external use only
- Do not spray directly into face
- Flammable: do not use near heat, flame, or while smoking

When using this product

- avoid spraying in eyes. If contact occurs, rinse thoroughly with water.
- do not puncture or incinerate. Contents under pressure. Do not store at temperatures above 120°F.

Stop use and ask a doctor if

irritation or rash develops

Keep out of reach of children.

If swallowed, get medical help or contact a Poison Control Center right away.

Directions

- apply generously and evenly to all areas 15 minutes before sun exposure
- spray on hands to apply to face
- use in well-ventilated area
- reapply at frequent intervals and after swimming or towel drying
- ask a doctor before use on children under six months of age

Other Information

Sun Alert: Limiting sun exposure, wearing protective clothing, and using sunscreens may reduce the risks of skin aging, skin cancer and other harmful effects of the sun. _ May stain some fabrics.

Inactive Ingredients

SD Alcohol 40-B, Acrylates/Octylacrylamide Copolymer, Caprylyl Glycol, Aloe Barbadensis Leaf Extract, Retinyl Palmitate (Vitamin A), Ascorbic Acid (Vitamin C), Tocopheryl Acetate (Vitamin E), PEG-8 Dimethicone, Sodium Propoxyhydroxypropyl, Thiosulfate Silica, Octyldodecanol, Silica, Fragrance.

Questions or Comments?

Call 1-800 SafeSun, Mon-Fri

MADE IN U.S.A.
Dist. by:
SUN PHARMACEUTICALS, LLC
SHELTON, CT 06484

PRINCIPAL DISPLAY PANEL

CLEAR
UltraMist®
BANANA
BOAT®
Ultra
Defense TM
Sheer Protect
Continuous Spray Sunscreen
SPF/UVB 30 with Aloe Vera
AvoTriplex TM
High UVA
Long-Lasting Protection
Sun-Tested, Sun-Proven TM
Lightweight & Rub-Free
Skin Cancer Foundation
Recommended
Very Water Resistant
6 FL. OZ. (177 mL)